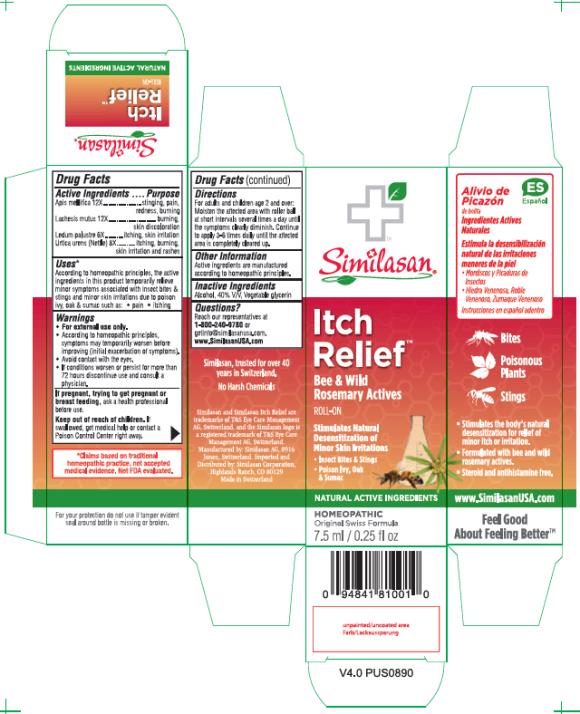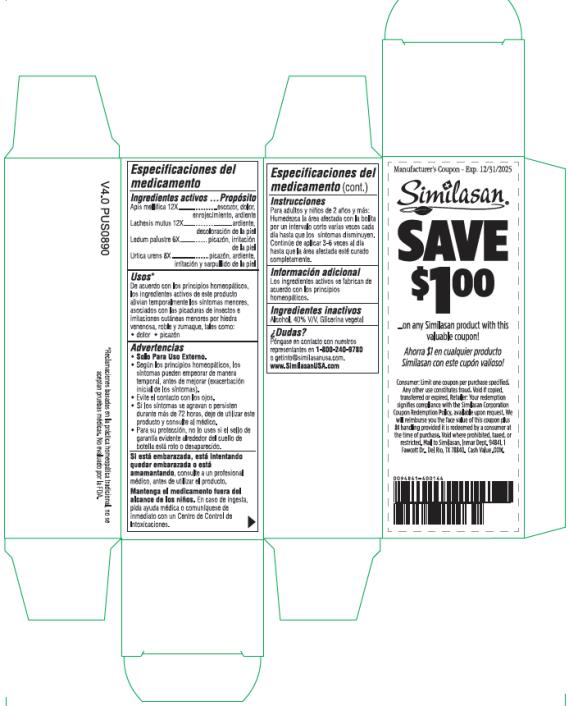 DRUG LABEL: Itch Relief
NDC: 53799-220 | Form: LIQUID
Manufacturer: Similasan AG
Category: homeopathic | Type: HUMAN OTC DRUG LABEL
Date: 20210426

ACTIVE INGREDIENTS: APIS MELLIFERA 12 [hp_X]/7.5 mL; LACHESIS MUTA VENOM 12 [hp_X]/7.5 mL; LEDUM PALUSTRE TWIG 6 [hp_X]/7.5 mL; URTICA URENS 8 [hp_X]/7.5 mL
INACTIVE INGREDIENTS: ALCOHOL; GLYCERIN

Itch Relief

Drug Facts

Active Ingredient

Apis mellifica 12X

Purpose

stinging, pain, redness, burning

Active Ingredient

Lachesis mutus 12X

Purpose

burning, skin discoloration

Active Ingredient

Ledum palustre 6X

Purpose

itching, skin irritation

Active Ingredient

Urtica urens 8X

Purpose

itching, burning, skin irritation and rashes

Uses:

According to homeopathic principles, the active ingredients in this product temporarily relieve minor symptoms associated with insect bites & stings and minor skin irritations due to poison ivy, oak & sumac such as: pain itching

Warnings:

- For external use only.
- According to homeopathic principles, symptoms may temporarily worsen before improving (initial exacerbation of symptoms).
- Avoid contact with the eyes.
- If conditions worsen or persist for more than 72 hours discontinue use and consult a physician.

If pregnant, trying to get pregnant or breast feeding,

ask a health professional before use.

Keep out of reach of children.

If swallowed, get medical help or contact a Poison Control Center right away.

Directions:

For adults and children age 2 and over: Moisten the affected area with roller ball at short intervals several times a day until the symptoms clearly diminish. Continue to apply 3-6 times daily until the affected area is completely cleared up.

Other Information:

Active ingredients are manufactured according to homeopathic principles.

Inactive Ingredients:

Alcohol, 40% V/V, Vegetable glycerin

Questions?

Reach our representatives at 1-800-240-9780 or getinfo@similasanusa.com.

www.SimilasanUSA.com

PRINCIPAL DISPLAY PANEL

Similasan®
Itch Relief
ROLL-ON
7.5 mL/0.25 fl oz